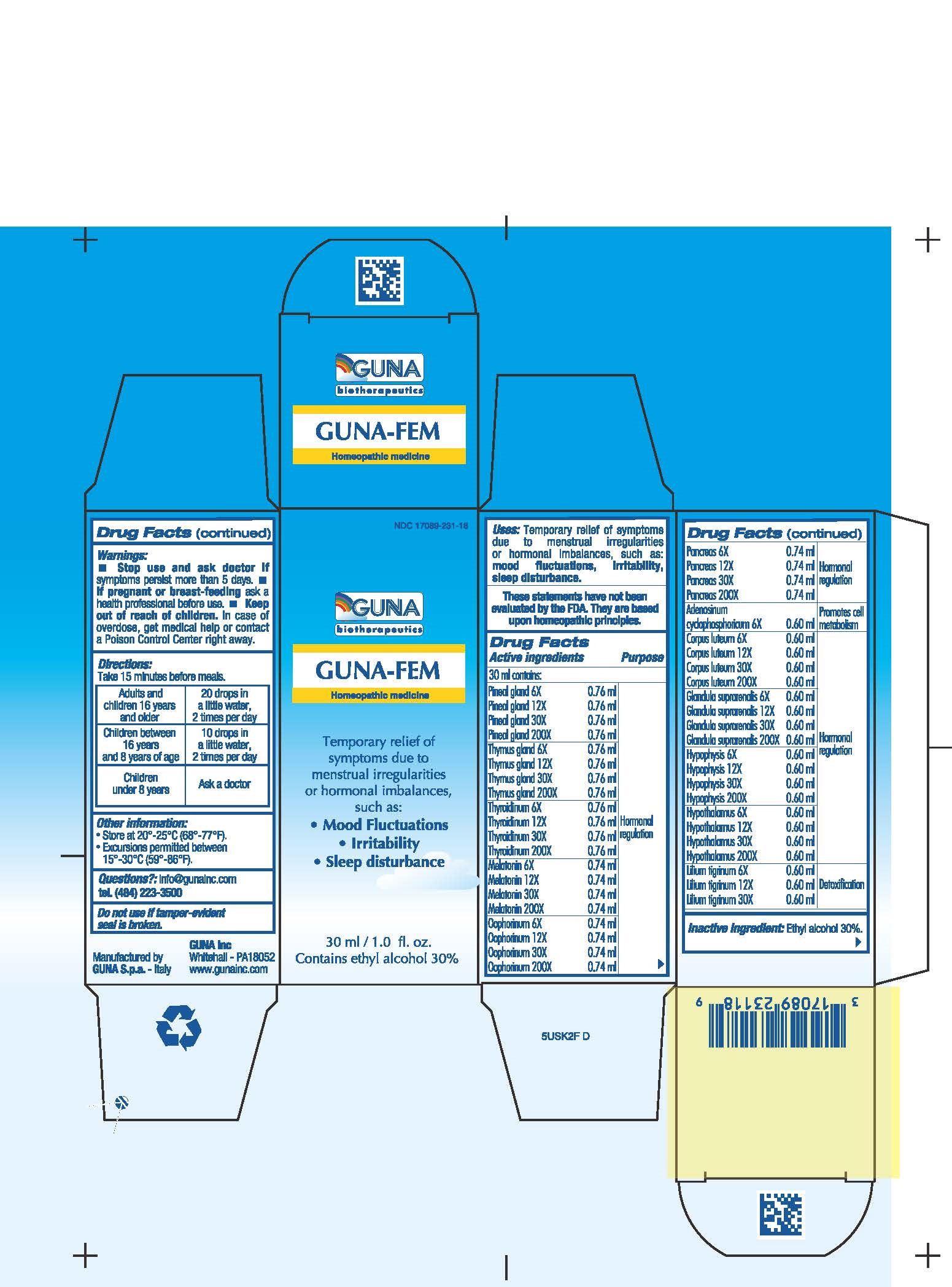 DRUG LABEL: GUNA-FEM
NDC: 17089-231 | Form: SOLUTION/ DROPS
Manufacturer: Guna spa
Category: homeopathic | Type: HUMAN OTC DRUG LABEL
Date: 20221114

ACTIVE INGREDIENTS: ADENOSINE CYCLIC PHOSPHATE 6 [hp_X]/30 mL; SUS SCROFA CORPUS LUTEUM 30 [hp_X]/30 mL; SUS SCROFA ADRENAL GLAND 30 [hp_X]/30 mL; SUS SCROFA PITUITARY GLAND 30 [hp_X]/30 mL; SUS SCROFA HYPOTHALAMUS 30 [hp_X]/30 mL; LILIUM LANCIFOLIUM BULB 6 [hp_X]/30 mL; MELATONIN 200 [hp_X]/30 mL; SUS SCROFA OVARY 6 [hp_X]/30 mL; SUS SCROFA PANCREAS 30 [hp_X]/30 mL; SUS SCROFA PINEAL GLAND 30 [hp_X]/30 mL; SUS SCROFA THYMUS 30 [hp_X]/30 mL; THYROID 6 [hp_X]/30 mL
INACTIVE INGREDIENTS: ALCOHOL 9 mL/30 mL

GUNA-FEM

ACTIVE INGREDIENTS/PURPOSE

ADENOSINUM CICLOPHOSPHORICUM 6X PROMOTES CELL METABOLISM
CORPUS LUTEUM 6X 12X 30X, 200X HORMONAL REGULATION
GLANDULA SUPRARENALIS 6X, 12X, 30X, 200X HORMONAL REGULATION
HYPOPHYSIS 6X, 12X, 30X, 200X HORMONAL REGULATION
HYPOTHALAMUS 6X, 12X, 30X, 200X HORMONAL REGULATION
LILIUM TIGRINUM 6X, 12X, 30X DETOXIFICATION
MELATONIN 6X, 12X, 30X, 200X HORMONAL REGULATION
OOPHORINUM 6X, 12X, 30X, 200X HORMONAL REGULATION
PANCREAS 6X, 12X, 30X, 200X HORMONAL REGULATION
PINEAL GLAND 6X, 12X, 30X, 200X HORMONAL REGULATION
THYMUS GLAND 6X, 12X, 30X, 200X HORMONAL REGULATION
THYROIDINUM 6X, 12X, 30X, 200X HORMONAL REGULATION

USES

Temporary relief of symptoms due to menstrual irregularities or hormonal imbalances, such as:

- Mood Fluctuations
- Irritability
- Sleep disturbance

WARNINGS

- Stop use and ask doctor if symptoms persist more than 5 days.
- If pregnant or breast-feeding ask a health professional before use.
- Keep out of reach of children. In case of overdose, get medical help or contact a Poison Control Center right away.
- Contains ethyl alcohol 30%

PREGNANCY

If pregnant or breast-feeding ask a doctor before use

WARNINGS

Keep out of reach of children

DIRECTIONS

Adults and children 16 years and older 20 drops in a little water 2 times per day
Children between 16 years and 8 years of age. 10 drops in a little water 2 times per day
Children under 8 years Ask a doctor

QUESTIONS

Questions?: info@gunainc.com
Tel. (484) 223-3500

Inactive ingredient: Ethyl alcohol 30%

INDICATIONS AND USAGE

Take 15 minutes before meals.